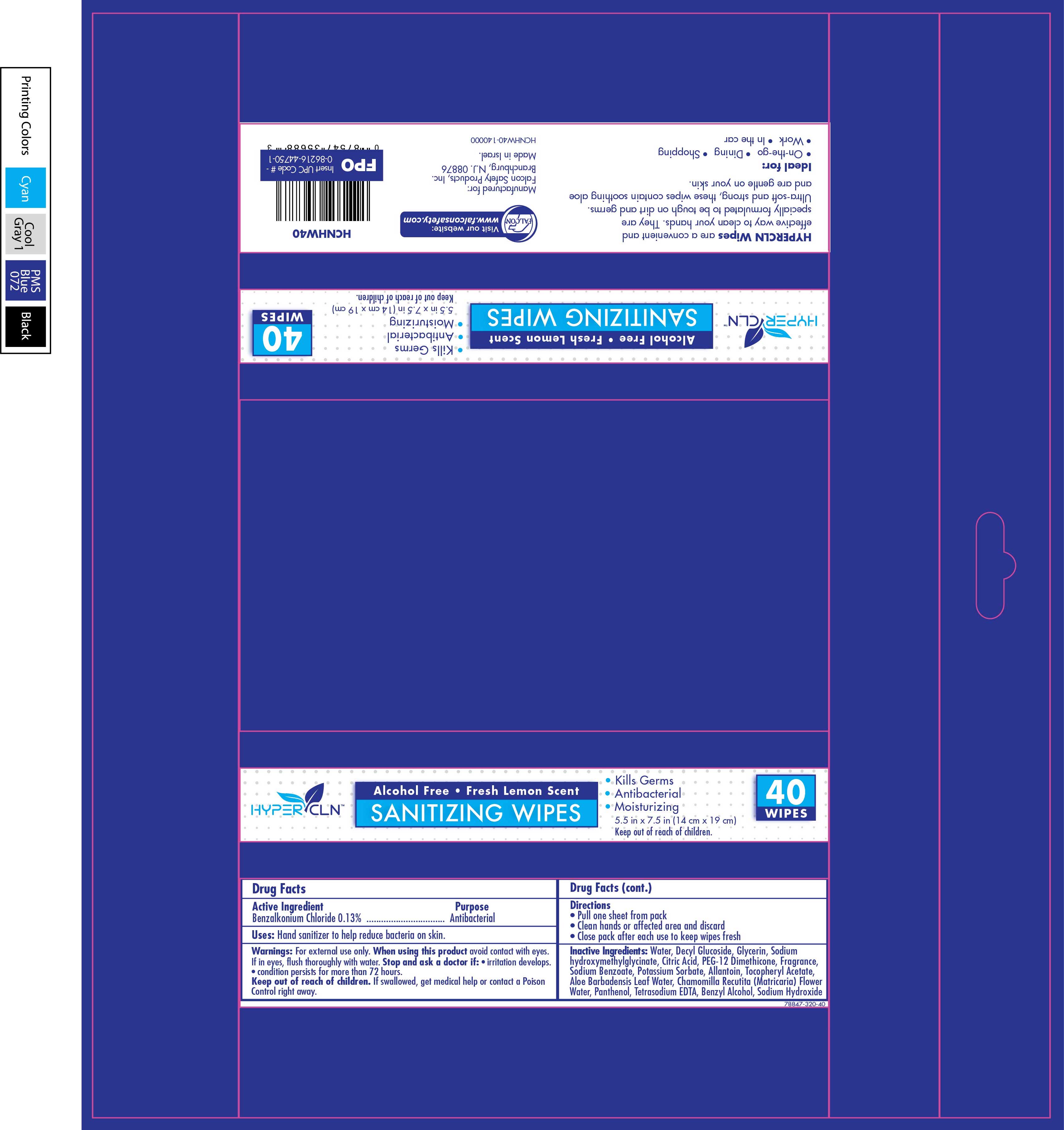 DRUG LABEL: Hypercln Sanitizing Wipes
NDC: 78847-320 | Form: CLOTH
Manufacturer: Falcon Safety Products, Inc.
Category: otc | Type: HUMAN OTC DRUG LABEL
Date: 20221027

ACTIVE INGREDIENTS: BENZALKONIUM CHLORIDE 0.0013 g/1 g
INACTIVE INGREDIENTS: POTASSIUM SORBATE; CHAMOMILE; TETRAHYDROLINALOOL; CITRONITRILE; EUCALYPTOL; SODIUM HYDROXYMETHYLGLYCINATE; ALLANTOIN; ALOE VERA LEAF; ANHYDROUS CITRIC ACID; PANTHENOL; WATER; PEG-12 DIMETHICONE (300 CST); DECYL GLUCOSIDE; EDETATE SODIUM; SODIUM BENZOATE; ALPHA-TOCOPHEROL ACETATE; GLYCERIN; 3,7-DIMETHYL-1-OCTANOL; 3,3'-DIHYDROXYDIPROPYL ETHER

Hypercln Sanitizing Wipes

Active Ingredient

Benzalkonium Chloride 0.13%

Purpose

Anti-bacterial

Warning

For external use only.

When using this product avoid contact with eyes. If in eyes, flush thoroughly with water.

Ask a doctor

Stop and ask a doctor if:

:• irritation develops. • condition persists for more than 72 hours.

Keep out of the reach of children.

Keep out of reach of children. If swallowed, get medical help or contact a Poison Control right away.

Dosage and Administration

Directions (for 40 ct flow pack)

• Pull one sheet from pack

• Clean hands or affected area and discard

• Close pack after each use to keep wipes fresh

Inactive ingredients

Water, Decyl Glucoside, Glycerin, Sodium hydroxymethylglycinate, Citric Acid, PEG-12 Dimethicone, Fragrance, Sodium Benzoate, Potassium Sorbate, Allantoin, Tocopheryl Acetate, Aloe Barbadensis Leaf Water, Chamomilla Recutita (Matricaria) Flower Water, Panthenol, Tetrasodium EDTA, Benzyl Alcohol, Sodium Hydroxide

Use

Hand sanitizer to help reduce bacteria on skin.